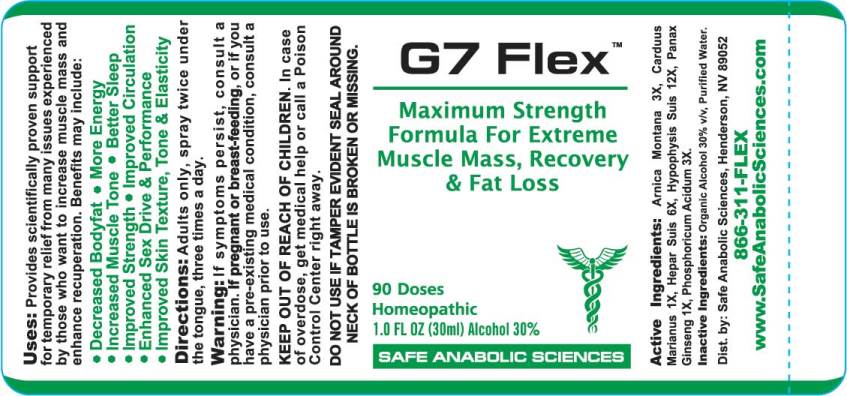 DRUG LABEL: G7 Flex
NDC: 49215-0009 | Form: LIQUID
Manufacturer: Safe Anabolic Sciences
Category: homeopathic | Type: HUMAN OTC DRUG LABEL
Date: 20180504

ACTIVE INGREDIENTS: ARNICA MONTANA 3 [hp_X]/1 mL; MILK THISTLE 1 [hp_X]/1 mL; PORK LIVER 6 [hp_X]/1 mL; SUS SCROFA PITUITARY GLAND 12 [hp_X]/1 mL; ASIAN GINSENG 1 [hp_X]/1 mL; PHOSPHORIC ACID 3 [hp_X]/1 mL
INACTIVE INGREDIENTS: WATER; ALCOHOL

Drug Facts:

ACTIVE INGREDIENTS:

Arnica Montana 3X, Carduus Marianus 1X, Hepar Suis 6X, Hypophysis Suis 12X, Panax Ginseng 1X, Phosphoricum Acidum 3X.

USES:

Provides scientifically proven support for temporary relief from many issues experienced by those who want to increase muscle mass and enhance recuperation. Benefits may include:

• Decreased Bodyfat • More Energy

• Increased Muscle Tone • Better Sleep

• Improved Strength • Improved Circulation

• Enhanced Sex Drive & Performance

• Improved Skin Texture, Tone & Elasticity

WARNINGS:

If symptoms persist, consult a physician.

If pregnant or breast-feeding, or if you have a pre-existing medical condition, consult a physician prior to use.

KEEP OUT OF REACH OF CHILDREN. In case of overdose, get medical help or call a Poison Control Center right away.

DO NOT USE IF TAMPER EVIDENT SEAL AROUND NECK OF BOTTLE IS BROKEN OR MISSING.

Keep out of reach of children. In case of overdose, get medical help or call a Poison Control Center right away.

DIRECTIONS:

Adults only, spray twice under the tongue, three times a day.

INDICATIONS:

Provides scientifically proven support for temporary relief from many issues experienced by those who want to increase muscle mass and enhance recuperation. Benefits may include:

• Decreased Bodyfat • More Energy
• Increased Muscle Tone • Better Sleep
• Improved Strength • Improved Circulation
• Enhanced Sex Drive & Performance

• Improved Skin Texture, Tone & Elasticity

INACTIVE INGREDIENTS:

Organic Alcohol 30% v/v, Purified Water

QUESTIONS:

Dist. by: Safe Anabolic Sciences, Henderson, NV 89052

866-311-FLEX

www.SafeAnabolicSciences.com

PACKAGE LABEL DISPLAY:

G7 FLEX

Maximum Strength

Formula For Extreme

Muscle Mass, Rapid Recovery

& Fat Loss

90 Doses

HOMEOPATHIC

1.0 FL OZ (30ml)

SAFE ANABOLIC SCIENCES